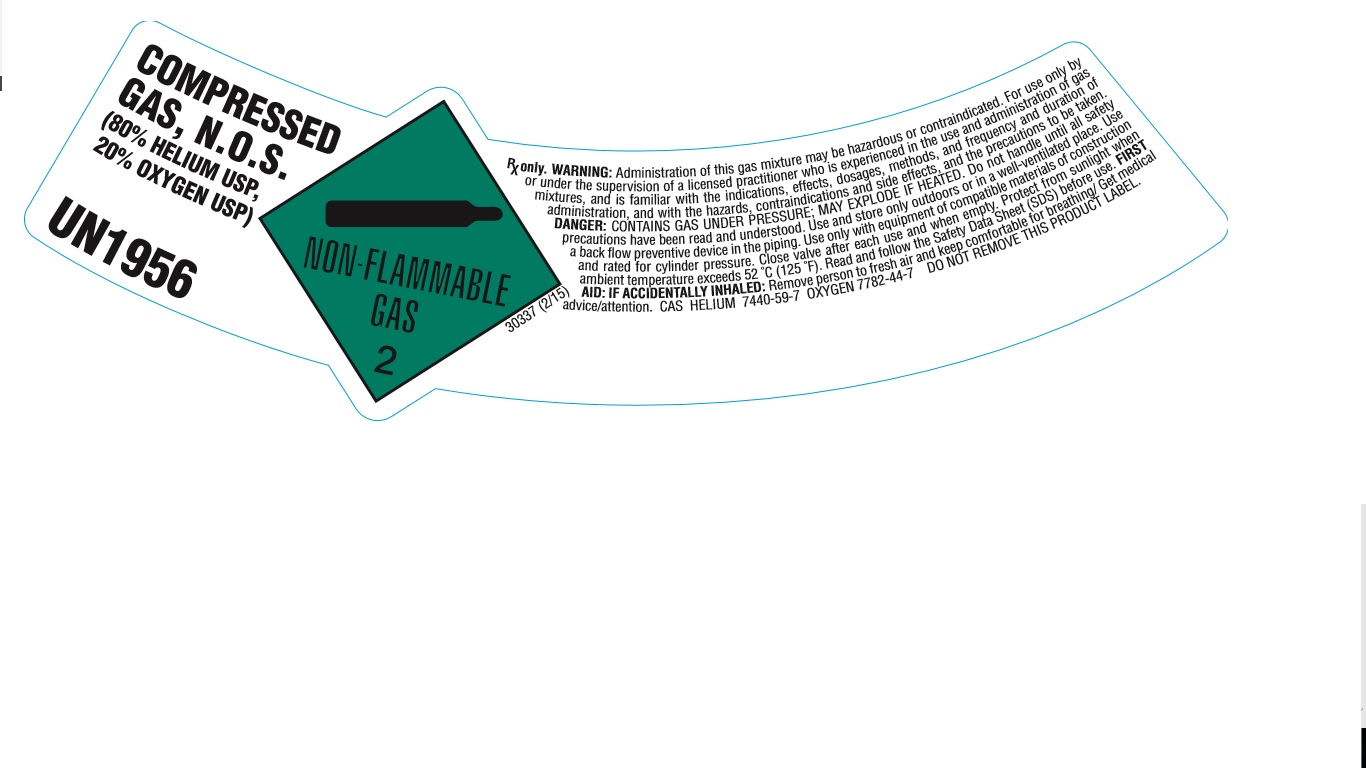 DRUG LABEL: Helium/Oxygen Mixture 80/20
NDC: 21220-155 | Form: GAS
Manufacturer: General Air Service & Supply Co.
Category: prescription | Type: HUMAN PRESCRIPTION DRUG LABEL
Date: 20251126

ACTIVE INGREDIENTS: OXYGEN 200 mL/1 L
INACTIVE INGREDIENTS: HELIUM 800 mL/1 L

Helium/Oxygen Mixture 80/20

PACKAGE LABEL

COMPRESSED GAS, N.O.S. (80% HELIUM USP, 20% OXYGEN USP)

UN1956

NON-FLAMMABLE GAS 2

RX only. WARNING: Administration of this gas mixture may be hazardous or contraindicated. For use only by or under the supervision of a licensed practitioner who is experienced in the use and administration of gas mixtures, and is familiar with the indications, effects, dosages, methods, and frequency and duration of administration, and with hazards, contraindications and side effects, and the precautions to be taken. DANGER: CONTAINS GAS UNDER PRESSURE; MAY EXPLODE IF HEATED. Do not handle until all safety precautions have been read and understood. Use and store only outdoors or in a well-ventilated place. Use a back flow preventive device in the piping. Use only with equipment of compatible materials of construction and rated for cylinder pressure. Close value after each use and when empty. Protect from sunlight when ambient temperature exceeds 52 degrees C (125 degrees F). Read and follow the Safety Data Sheet (SDS) before use. FIRST AID: IF ACCIDENTALLY INHALED: Remove person to fresh air and keep comfortable for breathing/ Get medical advice/attention. CAS HELIUM 7440-59-7 OXYGEN 7782-44-7 DO NOT REMOVE THIS PRODUCT LABEL